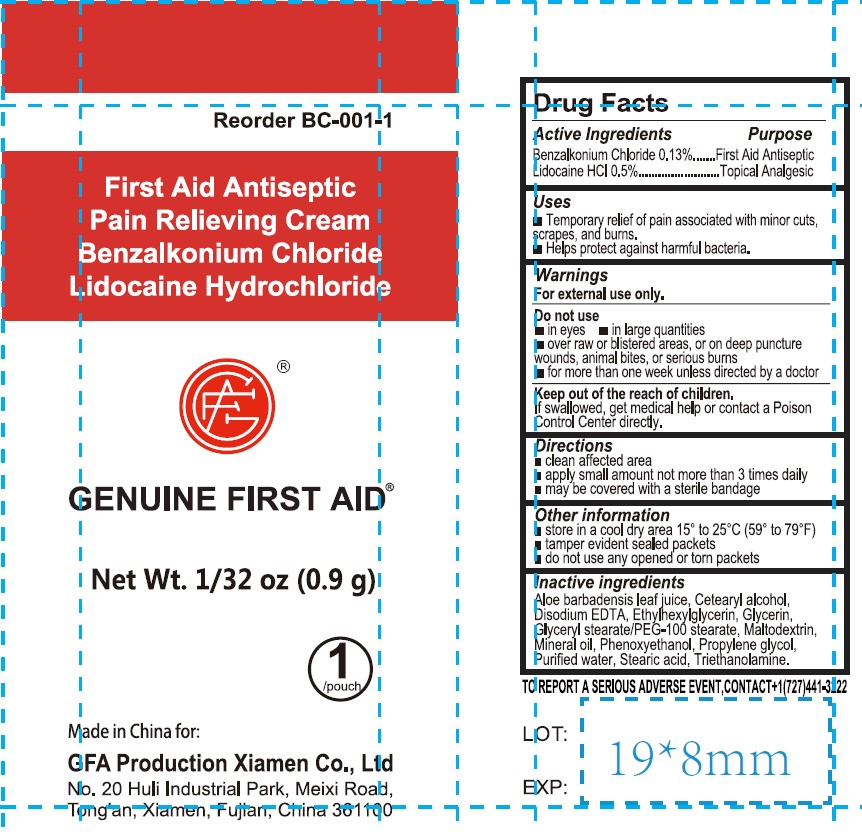 DRUG LABEL: GENUINE FIRST AID Antiseptic Pain Relieving
NDC: 43473-015 | Form: CREAM
Manufacturer: Nantong Health & Beyond Hygienic Products Inc.
Category: otc | Type: HUMAN OTC DRUG LABEL
Date: 20231019

ACTIVE INGREDIENTS: BENZALKONIUM CHLORIDE 0.13 g/100 g; LIDOCAINE HYDROCHLORIDE ANHYDROUS 0.5 g/100 g
INACTIVE INGREDIENTS: ALOE; GLYCERYL STEARATE/PEG-100 STEARATE; MINERAL OIL; PHENOXYETHANOL; STEARIC ACID; WATER; GLYCERIN; PROPYLENE GLYCOL; DISODIUM HEDTA; ETHYLHEXYLGLYCERIN; TRICLOSAN; MALTODEXTRIN

43473-015 Genuine First Aid Antiseptic Pain Relieving

Active ingredient

Benzalkonium Chloride 0.13%

Lidocaine HCL 0.5%

Purpose

First Aid Antiseptic

Topical Analgesic

Uses

Temporary relief of pain assocoated with minor cuts, scrapes, and burns.

Helps protect against harmful bacteria

Warnings

For external use only.

Do not use

- in eyes
- in large quantities
- over raw or blistered areas, or on deep puncture wounds, animal bites, or serious burns
- for more than one week unless directed by a doctor

Keep out of reach of children. If swallowed, get medical help or contact a Poison Control Center directly.

Directions

Clean affected area

Apply small amount not more than 3 times daily

Maybe covered with a sterile bandage

Other information

Store in a cool area 15C to 25C (59F to 77F)

Temper evident sealed packats

Do not use any opened or torn packets

Inactive ingredients

Aloe barbadensis leaf jiuce, Cetearyl Alcohol, Disodium EDTA, Ethylhexylglycerin, Glyceryl stearate/ PEG-100 Stearate, Glycerin, Maltodextrin, Mineral oil, Phenoxyethanol, Propylene glycol, Water, Stearic acid, Triethanolamine